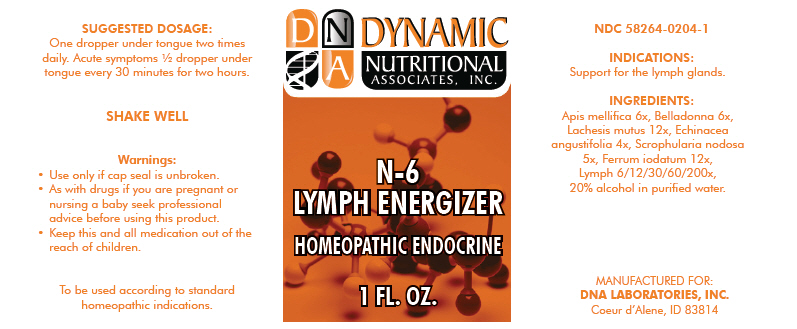 DRUG LABEL: N-6
NDC: 58264-0204 | Form: SOLUTION
Manufacturer: DNA Labs, Inc.
Category: homeopathic | Type: HUMAN OTC DRUG LABEL
Date: 20250109

ACTIVE INGREDIENTS: APIS MELLIFERA 6 [hp_X]/1 mL; ATROPA BELLADONNA 6 [hp_X]/1 mL; LACHESIS MUTA WHOLE 12 [hp_X]/1 mL; ECHINACEA ANGUSTIFOLIA 4 [hp_X]/1 mL; SCROPHULARIA NODOSA 5 [hp_X]/1 mL; FERROUS IODIDE 12 [hp_X]/1 mL; BOS TAURUS LYMPH 200 [hp_X]/1 mL
INACTIVE INGREDIENTS: ALCOHOL; WATER

N-6

NDC 58264-0204-1

INDICATIONS AND USAGE

INDICATIONS

Support for the lymph glands.

ACTIVE INGREDIENT

INGREDIENTS

Apis mellifica 6x, Belladonna 6x, Lachesis mutus 12x, Echinacea angustifolia 4x, Scrophularia nodosa 5x, Ferrum iodatum 12x, Lymph 6/12/30/60/200x, 20% alcohol in purified water.

SUGGESTED DOSAGE

One dropper under tongue two times daily. Acute symptoms ½ dropper under tongue every 30 minutes for two hours.

STORAGE AND HANDLING

SHAKE WELL

Warnings

- Use only if cap seal is unbroken.

PREGNANCY OR BREAST FEEDING

- As with drugs if you are pregnant or nursing a baby seek professional advice before using this product.

KEEP OUT OF REACH OF CHILDREN

- Keep this and all medication out of the reach of children.

To be used according to standard homeopathic indications.

PRINCIPAL DISPLAY PANEL - 1 FL. OZ. Bottle Label

DYNAMIC
NUTRITIONAL
ASSOCIATES, INC.

N-6

LYMPH ENERGIZER

HOMEOPATHIC ENDOCRINE

1 FL. OZ.